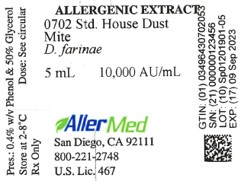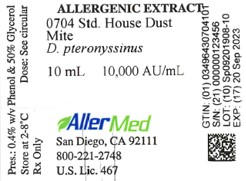 DRUG LABEL: House Dust Mite, Dermatophagoides farinae
NDC: 49643-702 | Form: INJECTION
Manufacturer: Allermed Laboratories, Inc.
Category: prescription | Type: HUMAN PRESCRIPTION DRUG LABEL
Date: 20250603

ACTIVE INGREDIENTS: DERMATOPHAGOIDES FARINAE 10000 [AU]/1 mL
INACTIVE INGREDIENTS: SODIUM CHLORIDE 0.0025 g/1 mL; SODIUM BICARBONATE 0.00125 g/1 mL; GLYCERIN 0.53 g/1 mL; PHENOL 0.004 g/1 mL; WATER

ALLERGENIC EXTRACT Standardized Mite Dermatophagoides farinae and Dermatophagoides pteronyssinus

WARNINGS

This product is intended for use by physicians who are experienced in the administration of allergenic extracts or for use under the

guidance of an allergy specialist. The initial dose must be based on skin testing as described in the dosage and administration section of this insert. Patients being switched from alum-absorbed or other types of precipitated extracts or non-standardized extracts to this extract should be started as though they were coming under treatment for the first time. Patients should be instructed to
recognize adverse reaction symptoms and cautioned to contact the physician's office if symptoms occur. As with all allergenic extracts, severe systemic reactions may occur and in certain individuals, especially steroid dependent/liable asthmatics, these reactions maybe life-threatening or cause death (11). Patients should be observed for at least 20 minutes following treatment. Emergency measures as well as personnel trained in their use should be immediately available in the event of a life-threatening reaction. Patients being switched from one lot of extract to another from the same manufacturer should have the dose reduced to 25 percent.

Patients receiving beta-blocking drugs may be refractive to the usual dose of epinephrine, in the event that epinephrine is required to control an adverse allergic reaction to this product.

This product should never be injected intravenously. See also the WARNINGS, and ADVERSE REACTIONS sections below.

Serious adverse reactions to this product should be reported to MEDWATCH, Food and Drug Administration, 5600 Fishers Lane, MD 20852-9787. Telephone 1-800-822-7967 or www.vaers.hhs.gov.

DESCRIPTION

Mite extract is a sterile solution containing the extractables of mite whole bodies in 0.25% sodium chloride, 0.125% sodium bicarbonate, 50% glycerol by volume and 0.4% phenol as a preservative. The mites are grown on a medium of yeast and pork and are handled and cleaned in a manner to remove more than 99% of the food medium. The medium contains no material of human origin. This extract may be administered by the scratch, prick-puncture, or intradermal methods of skin testing for diagnostic purposes and subcutaneously for therapeutic purposes as directed under Dosage and Administration.

Intradermal skin tests in patients who were puncture test positive (Sum E ≥ 40 mm) to either D. farinae or D. pteronyssinus extract were performed with extracts of the mite food medium obtained from the same supplier. The results, submitted to the FDA by several manufacturers, were as follows: By intradermal testing, there was 1 positive (Sum E ≥ 20 mm) in 44 individuals at an estimated 1% level of medium content (approximately the same as contained in the mite extract). At a ten-fold increase (estimated 10% medium content), 4 positives in 40 individuals were observed. Two of the individuals who were skin test positive to the mite extract and
who also were skin test positive to the medium extract were also skin test positive to an extract of yeast (Saccharomyces sp.) when tested by the puncture method.

The extract is standardized by comparing its relative potency by ELISA competition to a U.S. reference mite extract available from the Center for Biologics Evaluation and Research, U.S. Food and Drug Administration. The U.S. reference extract has been assigned a potency of 10,000 AU/mL based on quantitative skin testing (1).

CLINICAL PHARMACOLOGY

The mechanism for the pharmacologic action of allergenic extracts used diagnostically is based on the liberation of histamine and other substances when the allergen reacts with IgE antibody attached to mast cells. The mechanism of the therapeutic effect is not well understood and further research is required to substantiate current hypotheses.

Mites belonging to the genus Dermatophagoides are found in approximately 80% of house dust samples throughout the world (2,3). D. farinae is common in much of the United States (3), although D. pteronyssinus is predominant in certain coastal regions and both species are commonly found in homes (4,5).

The diagnosis of mite allergy is established by the allergy history and skin test reactivity (6,7).

Immunotherapy with mite extract has been studied by several investigators. It is generally believed that hyposensitization with this product is helpful in reducing symptoms associated with house dust allergy (8,9).

INDICATIONS AND USAGE

Standardized mite extract is indicated for use in the diagnosis of patients with a history of allergy to mites or house dust and for the treatment of patients with a history of mite allergy who have established sensitivity to mites by diagnostic skin testing.

The use of mite extract for the above purposes should be made only by physicians with special familiarity and knowledge of allergy as described in a standard allergy textbook (10).

CONTRAINDICATIONS

Injections of mite extract should not be administered in the presence of diseases characterized by a bleeding diathesis. Immunotherapy should not be started in patients until a specific diagnosis of Type I allergy to mite is made by a physician based on skin testing with this product.
Other contraindications include:

EXTREME SENSITIVITY TO MITE: Determined from previous anaphylaxis following skin testing, immunotherapy, or natural exposure.
AUTOIMMUNE DISEASE: Individuals with autoimmune disease maybe at risk, due to the possibility of routine immunizations exacerbating symptoms of the underlying disease.
MYOCARDIAL INFARCTION: Patients who have experienced a recent myocardial infarction may not be able to tolerate immunotherapy. The benefit-to-risk ratio must be carefully evaluated.
CHILDREN WITH NEPHROTIC SYNDROME: Children with nephrotic syndrome require careful consideration and probably should not receive immunotherapy due to a variety of seemingly unrelated events that may cause an exacerbation of nephrotic disease.

WARNINGS

Concentrated extract must be diluted with sterile diluent prior to first use on a patient for treatment or intradermal testing. All concentrates of allergenic extract are manufactured to assure high potency and therefore have the ability to cause serious local and systemic reactions, including death in sensitive patients (11). Patients should be informed of this risk and precautions should be discussed prior to initiating immunotherapy (see PRECAUTIONS below).

Allergenic extract should be temporarily withheld from patients or the dose adjusted downward if any of the following conditions exist: 1) severe symptoms of rhinitis and/or asthma; 2) infection or flu accompanied by fever; 3) exposure to excessive amounts of clinically relevant allergen prior to a scheduled injection.

The dosage must be reduced when starting a patient on fresh standardized mite extract or when transferring a patient from non-standardized or modified extract to standardized extract, even though the labeled strength of the old and new vials may be the same. This is necessary due to a loss of extract potency during storage in the physician's office. The mite allergen content of old and new extract may be compared and adjusted by dosage reduction and/or dilution before the new extract is administered.

The amount of new extract given should not exceed 25% of the last dose given from the old vial, assuming both extracts contain comparable amounts of mite allergen. Any evidence of a local or generalized reaction requires a reduction in dosage during the initial stages of immunotherapy, as well as during maintenance therapy.

Beta-blocking drugs may make patients refractory to the usual dose of epinephrine, in the event epinephrine is required to treat an adverse allergic reaction.

PRECAUTIONS

GENERAL: This product should not be injected intravenously. The risk of severe allergic reactions can be minimized by taking a careful history and by the use of scratch or prick-puncture testing prior to intradermal testing. If the scratch or prick-puncture test is negative, an intradermal test with a one hundred-fold dilution of the concentration used for scratch or prick tests usually is safe. If there is a history of unusual sensitivity or if the scratch or prick-puncture test is not performed first, a more dilute solution such as 1:10,000 v/v of the concentrate should be used initially for intradermal testing. Systemic allergic reactions may occur as a result of immunotherapy. The risk can be minimized by adherence to a careful injection schedule, which starts with a low concentration of extract and is increased slowly. The physician must be prepared to treat anaphylaxis should it occur and have the necessary drugs and equipment on hand to do so. Extracts should not be administered by the patient or other individuals who are not prepared to
treat anaphylaxis should it occur. A separate sterile tuberculin syringe graduated in 0.01 mL should be used for each injection.
Antihistamines and hydroxyzine can significantly inhibit the immediate skin test reaction (see DRUG INTERACTION).

INFORMATION FOR PATIENTS: Because most serious reactions following the administration of allergenic extracts occur within 20 minutes of the injection, the patient should remain under observation for this period of time. The size of the local reaction should be recorded, because increasingly large local reactions may precede a subsequent systemic reaction with increasing dosage. The patient should be instructed to report any unusual reactions to the attention of the physician. In particular, this includes swelling and/or tenderness at the injection site or reactions such as rhinorrhea, sneezing, coughing, wheezing, shortness of breath, nausea,
dizziness or faintness. Caution should be exercised in testing or treating pregnant females because a systemic reaction might conceivably cause uterine muscle contractions leading to abortion.

CARCINOGENESIS, MUTAGENESIS, IMPAIRMENT OF FERTILITY: Long term studies in animals have not been conducted with allergenic extracts to determine their potential for carcinogenicity, mutagenicity or impairment of fertility.

PREGNANCY CATEGORY C: Animal reproduction studies have not been conducted with mite extract. It is also not known whether mite extract can cause fetal harm when administered to a pregnant woman or can affect reproduction capacity. Mite extract should be given to a pregnant woman only if clearly needed.

NURSING MOTHERS: It is not known whether allergenic extracts are excreted in human milk. Because many drugs are excreted in human milk caution should be exercised when allergenic extracts are administered to a nursing woman.

PEDIATRIC USE: Although standardized mite extract has not been studied in children, unstandardized extract of D. farinae has been administered by the prick test to asthmatic children ages 1 to 16 without any reported adverse response (6). Extract of D. pteronyssinus has been given subcutaneously for hyposensitization to children ages 5 to 14 with adverse reactions being limited to local discomfort, redness and swelling for one or two days (7).

DRUG INTERACTION: Antihistamines and hydroxyzine can inhibit the immediate skin test reaction. Patients being treated with delayed absorption antihistamine tablets should be free of such medication for 48 hours before testing. Non-sedating antihistamines, such as terfinadine and astemizole, may variably suppress the skin response for longer periods of time. Epinephrine injection inhibits the immediate skin test reaction for several hours. Beta-blocking drugs may make patients refractory to the usual dose of epinephrine, in the event epinephrine is required to treat an adverse allergic reaction.

ADVERSE REACTIONS

Adverse systemic reactions usually occur within minutes and consist primarily of allergic symptoms such as generalized skin erythema, urticaria, pruritus, angioedema, rhinitis, wheezing, laryngeal edema and hypotension. Less commonly, nausea, emesis, abdominal cramps, diarrhea and uterine contractions may occur. Severe reactions may cause shock and loss of consciousness. Fatalities have occurred rarely (11). Systemic reactions occur with varying frequency in different clinics. To some extent, the reaction rate is related to the type and dose of administered extract and to the degree of sensitivity of the patient. Despite all precautions, occasional reactions are unavoidable.

Reports from regulatory authorities in Sweden to the Center for Biologics Evaluation and Research (CBER) indicated that several deaths have been associated with the use of mite extracts. CBER was subsequently informed that these deaths may have been related to use by physicians or other health professionals untrained in the administration of potent allergens, rather than a product defect. It should be noted that anaphylaxis and deaths following the injection of mite and other extracts also have been reported by the British Committee on Safety in Medicine in the British Medical Journal, 293:943, 1986.

Local reactions consisting of erythema, itching, swelling, tenderness and sometimes pain may occur at the injection site. These reactions may appear within a few minutes to hours and persist for several days. Local cold applications and oral antihistamines may be effective treatment. For marked and prolonged local reactions, steroids may be helpful.

The treatment of systemic allergic reactions is somewhat dependent upon the symptom complex. Epinephrine hydrochloride 1:1,000 aqueous, in an adult dose of 0.3 - 0.5 mL (or 0.01 mL per kg. for children) administeredsubcutaneously in the opposite arm is the immediate treatment of choice. A tourniquet should be placed above the site of the extract injection if the injection was done on the extremities. Antihistamines may offer relief of recurrent urticaria, associated skin reactions and gastrointestinal symptoms. Persistent wheezing may necessitate intravenous aminophylline treatment. For profound shock and hypotension, intravenous fluids, vasopressors and oxygen also may be needed. Maintenance of an open airway is critical if upper airway obstruction is present. Corticosteroids may provide benefit if symptoms are prolonged or recurrent.

OVERDOSAGE

A strong local reaction to the injection of extract may be treated with oral antihistamines and the local application of a cold compress. The dosage must be reduced and additional extract must not be given until all evidence of the reaction has disappeared. A systemic reaction following the injection of extract must be treated immediately with Epinephrine hydrochloride 1:1,000 aqueous (see Adverse Reactions, paragraph 4 above).

DOSAGE AND ADMINISTRATION

Parenteral drug products should be inspected visually for particulate matter and discoloration prior to administration, whenever solution and container permit. The product should be discarded if discoloration or particles are observed.

DIAGNOSTIC USE:

Percutaneous Tests: The skin test concentration of 10,000 AU/mL in dropper vials is used for scratch or prick-puncture testing. Puncture tests performed with D. farinae extract on 5 persons sensitive to mite showed a mean diameter wheal of 8.8 mm ± 1.8 mm and mean diameter erythema of 39.2 mm ± 5.3 mm. Puncture tests with D. pteronyssinus extract on 10 persons sensitive to
mite showed a mean diameter wheal of 7.8 mm ± 4.1 mm and mean erythema of 33.7 mm ± 12.0 mm.

Intradermal Tests: Extract for intradermal testing should be prepared by diluting the 10,000 AU/mL stock concentrate in bulk vials with sterile saline with or without human serum albumin. Intradermal skin tests (0.05 mL) in persons highly sensitive to mite
showed the following results:

Table 1 AU/mL to elicit 50 mm sum of diameter erythema reaction
Allergen | No. of Persons | Mean | Range
D. farinae | 5 | 0.0040 | 0.0013-0.0124
D. pteronyssinus | 10 | 0.0031 | 0.0001-0.1416

Intradermal tests should only be performed after a scratch or prick-puncture test has been administered with a negative result.

Patients who do not react to a valid scratch or prick-puncture test should be tested intradermally with 0.02 to 0.05 mL of a 10 AU/mL (1:1,000 v/v of the 10,000 AU/mL concentrate). If this test is negative, a second intradermal test may be performed using a 100 AU/mL (1:100 v/v dilution of 10,000 AU/mL concentrate).

Skin tests are graded in terms of the wheal and erythema response noted at 15 to 20 minutes. Wheal and erythema size may be recorded by actual measurement of the extent of both responses.

THERAPEUTIC USE: The dosage of mite extract administered by subcutaneous injection is highly individualized and varies according to the degree of sensitivity of the patient, his clinical response and tolerance to the extract administered during the early phases of an injection regimen. In patients who appear to be highly sensitive by history and skin test, the initial dose of the extract should be 0.05 mL of a 0.1 AU/mL dilution or as established by skin test titration. The amount of allergenic extract is increased at each injection by not more than 50% - 100% of the previous amount, and the next increment is governed by the response to the last injection. Large local reactions which persist for longer than 24 hours are generally considered an indication for repeating the previous dose or reducing the dose. Any evidence of systemic reaction is an indication for a significant reduction (at least 50%) in the subsequent dose. The upper limits of dosage have not been established; however, doses larger than 0.2 mL of the concentrate may be painful due to the glycerin content of the extract. The optimal interval between doses of mite extract has not been definitely established. However, as is customarily practiced, injections are given one or two times per week until the maintenance dose of extract is reached. At this time, the injection interval may be increased to 2 weeks, then to 3 weeks and finally to 4 weeks. If the patient does not return for 6 to 8 weeks after the last injection, the dose should be reduced to 25% of the last dose. If longer than 8 weeks, a dose reduction of one, two or three dilutions may be made depending on a consideration of the components and the patient's sensitivity The dosage and the interval between injections may need to be modified according to the clinical response of the patient. When switching patients to fresh extract, the initial dose should be reduced to one-quarter (25%) of the previous dose.

The usual duration of treatment has not been established. A period of three to five years of injection therapy constitutes an average course of treatment.

Children and older age patients appear to tolerate injections of allergenic extract well, and no special recommendations need to be made for these groups.

PREPARING DILUTIONS

To prepare dilutions for intradermal skin tests and therapeutic use as shown in the table below, make a series of ten-fold dilutions starting with the 5,000 AU/mL or 10,000 AU/mL as follows: add 1.0 mL of the concentrate to 9.0 mL of sterile diluent to make the 1:10 dilution; add 1.0 mL of the 1:10 dilution to 9.0 mL of sterile diluent to make the 1:100 dilution. Continue making dilutions as shown in the table below until the highest desired dilution is reached. The number of allergy units per mL in each dilution is shown in the table below.

Table 2 Volume per volume dilutions of 5,000 AU/mL and 10,000 AU/mL concentrates to provide a ten-fold dilution series.
Vial No. | w/v Dilution of Concentrate | 5,000 AU/mL Concentrate AU/mL | 10,000 AU/mL Concentrate AU/mL
1 | 1:100,000 | 0.05 | 0.1
2 | 1:10,000 | 0.5 | 1
3 | 1:1,000 | 5 | 10
4 | 1:100 | 50 | 100
5 | 1:10 | 500 | 1,000
6 | No Dilution | 5,000 | 10,000

HOW SUPPLIED

Extract of D. farinae and D. pteronyssinus containing 5,000 and 10,000 Allergy Units per mL is supplied in 50% glycerol v/v in 10 mL, 30 mL and 50 mL vials. Extract containing 10,000 Allergy Units per mL is supplied in 50% glycerol v/v in dropper vials for scratch or prick-puncture testing. An equal v/v mixture of the two mites is offered in 10, 30 and 50 mL vial sizes at a concentration of 2,500 AU/mL or 5,000 AU/mL for each mite. See DESCRIPTION above for the complete list of the active and inactive ingredients of this product.
Extract of D. farinae and D. pteronyssinus may be diluted in sterile buffered saline containing 0.4% phenol or in sterile buffered saline containing human serum albumin and 0.4% phenol.

STORAGE AND HANDLING

Extract should be stored at 2-8°C since higher temperatures may adversely affect stability. Do not freeze.

REFERENCES

1. Turkeltaub, P.C. The allergy unit-clinical relevance: issues in allergen standardization. In: R.F. Lockey, S.C. Bukantz, eds. Allergen
Immunotherapy. New York, NY: Marcel Dekker, Inc., 171-190, 1991.
2. Wharton, G.W. House dust mites. J. Med. Entomol., 12:577, 1976.
3. Voorhost, R., Spieksma, F.Th.M., and Varekamp, H. House dust atopy and the house mite. Leiden, Stafleu's Scientific Publishing Co., 1969.
4. Baer, H. Allergy to house dust mites. Immuno. Allergy Practice, 5:356, 1983.
5. Lang, J.D. and Mulla, S. Distribution and abundance of house dust mites, Dermatophagoides (spp.) in different zones of Southern
California. Environmental Entomology, 6:213, 1977.
6. Pauli, G., Bessot, J.C., Thierry, R. and Lamensans, A. Correlation between skin tests, inhalation tests and specific IgE in a study of 120 subjects allergic to house dust and D. pteronyssinus . Clin. Allergy, 7:337, 1977.
7. Murray, A.B., Ferguson A.C. and Morrison, B.J. Diagnosis of house dust mite allergy in asthmatic children. What constitutes a positive history? J. Allergy Clin. Immunol., 71:21, 1983.
8. Warner, J.O., Price, J.F., Soothill, J.F. and Hey, E.N. Controlled trial of hyposensitization to D. pteronyssinus in children with asthma. Lancet, 2:912, 1978.
9. Smith, A.P., Hyposensitization with D. pteronyssinus antigen. Trial in asthma induced by house dust. Br. Med. J., 4:204, 1971.
10. Middleton, E. Jr., Reed, C.E., Ellis, F.E., Adkinson, N.F. Jr., Yunginger, J.W., Busse, W.W. Allergy Principles and Practice, 4th Ed., Vol II, 963-982, Mosey, St. Louis, 1993.
11. Reid, M.J., Lockey, R.F., Turkeltaub, P.C., Platts-Mills, T.A.E. Survey of fatalities from skin testing and immunotherapy 1985-1989. J. Allergy Clin. Immunol., 92:6, 1993.